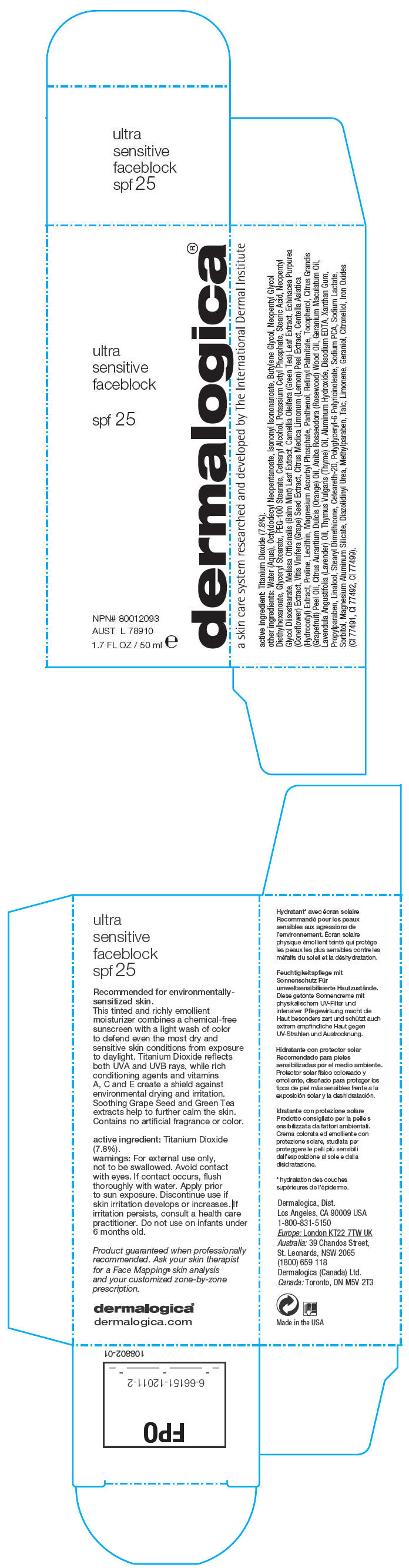 DRUG LABEL: Ultra Sensitive Faceblock SPF 25
NDC: 21839-011 | Form: LOTION
Manufacturer: Gordon Laboratories, Inc
Category: otc | Type: HUMAN OTC DRUG LABEL
Date: 20110803

ACTIVE INGREDIENTS: Titanium Dioxide 4000 mg/50 mL
INACTIVE INGREDIENTS: Water; Octyldodecyl Neopentanoate; Isononyl Isononanoate; Butylene Glycol; Neopentyl Glycol Diethylhexanoate; Glyceryl Monostearate; PEG-100 Stearate; Cetostearyl Alcohol; Potassium Cetyl Phosphate; Stearic Acid; Neopentyl Glycol Disostearate; Melissa Officinalis Leaf; Camellia Oleifera Leaf; Echinacea Purpurea; Vitis Vinifera Seed; Lemon Peel; Centella Asiatica; Proline; Magnesium Ascorbyl Phosphate; Panthenol; Vitamin A Palmitate; Tocopherol; Citrus Maxima Fruit Rind Oil; Rosewood Oil; Lavender Oil; Thyme Oil; Aluminum Hydroxide; Edetate Disodium; Xanthan Gum; Propylparaben; Linalool, (+/-)-; Polyoxyl 20 Cetostearyl Ether; Sodium Pyrrolidone Carboxylate; Sodium Lactate; Sorbitol; Magnesium Aluminum Silicate; Diazolidinyl Urea; Methylparaben; Talc; Geraniol; FERRIC OXIDE RED; FERRIC OXIDE YELLOW; FERROSOFERRIC OXIDE

dermalogica®
ultra
sensitive
faceblock

active ingredient

Titanium Dioxide (7.8%).

warnings

For external use only, not to be swallowed. Avoid contact with eyes. If contact occurs, flush thoroughly with water. Apply prior to sun exposure.

STOP USE

Discontinue use if skin irritation develops or increases. If irritation persists, consult a health care practitioner.

Do not use on infants under 6 months old.

other ingredients

Water (Aqua), Octyldodecyl Neopentanoate, Isononyl Isononanoate, Butylene Glycol, Neopentyl Glycol Diethylhexanoate, Glyceryl Stearate, PEG-100 Stearate, Cetearyl Alcohol, Potassium Cetyl Phosphate, Stearic Acid, Neopentyl Glycol Diisostearate, Melissa Officinalis (Balm Mint) Leaf Extract, Camellia Oleifera (Green Tea) Leaf Extract, Echinacea Purpurea (Coneflower) Extract, Vitis Vinifera (Grape) Seed Extract, Citrus Medica Limonum (Lemon) Peel Extract, Centella Asiatica (Hydrocotyl) Extract, Proline, Lecithin, Magnesium Ascorbyl Phosphate, Panthenol, Retinyl Palmitate, Tocopherol, Citrus Grandis (Grapefruit) Peel Oil, Citrus Aurantium Dulcis (Orange) Oil, Aniba Rosaeodora (Rosewood) Wood Oil, Geranium Maculatum Oil, Lavendula Angustifolia (Lavender) Oil, Thymus Vulgaris (Thyme) Oil, Aluminum Hydroxide, Disodium EDTA, Xanthan Gum, Propylparaben, Linalool, Stearyl Dimethicone, Ceteareth-20, Polyglyceryl-6 Polyricinoleate, Sodium PCA, Sodium Lactate, Sorbitol, Magnesium Aluminum Silicate, Diazolidinyl Urea, Methylparaben, Talc, Limonene, Geraniol, Citronellol, Iron Oxides (CI 77491, CI 77492, CI 77499).

Dermalogica, Dist.
Los Angeles, CA 90009 USA
1-800-831-5150

PRINCIPAL DISPLAY PANEL - 50 mL Bottle Carton

dermalogica®

ultra
sensitive
faceblock

spf 25

NPN# 80012093
AUST L 78910

1.7 FL OZ / 50 ml e